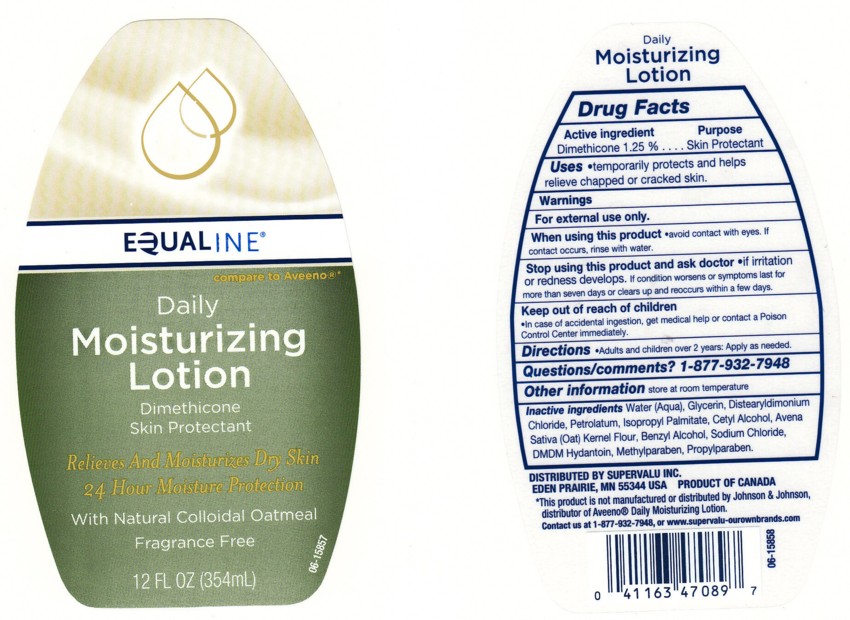 DRUG LABEL: DAILY MOISTURIZING 
NDC: 41163-320 | Form: LOTION
Manufacturer: SUPERVALU INC
Category: otc | Type: HUMAN OTC DRUG LABEL
Date: 20100721

ACTIVE INGREDIENTS: DIMETHICONE 1.2500 mL/100 mL

BACK LABEL - DRUG FACTS BOX

ACTIVE INGREDIENT

DIMETHICONE 1.25%

WARNING

FOR EXTERNAL USE ONLY.

WHEN USING THIS PRODUCT

AVOID CONTACT WITH EYES, IF CONTACT OCCURS, RINSE EYE THROUGHLY WITH WATER.

STOP USING THIS PRODUCT AND ASK A DOCTOR IF

CONDITION WORSENS OR SYMPTOMS PERSIST FOR MORE THAN SEVEN DAYS OR OCCUR AGAIN WITHIN A FEW DAYS.

KEEP OUT OF REACH OF CHILDREN

IN CASE OF ACCIDENTAL INGESTION, GET MEDICAL HELP OR CONTACT A POISON CONTROL CENTER IMMEDIATELY.

PURPOSE

SKIN PROTECTANT

QUESTIONS/COMMENTS?

1 - 877 - 932 - 7948

DIRECTIONS

ADULTS AND CHILDREN OVER 2 YEARS: APPLY AS NEEDED.

USES

TEMPORARILY PROTECTS AND HELPS RELIEVE CHAPPED OR CRACKED SKIN.

INACTIVE INGREDIENTS

WATER (AQUA), GLYCERIN, DISTEARYLDIMONIUM CHLORIDE, PETROLATUM, ISOPROPYL PALMITATE, CETYL ALCOHOL, AVENA SATIVA (OAT) KEMEL FLOUR, BENZYL ALCOHOL, SODIUM CHLORIDE, DMDM HYDANTOIN, METHYLPARABEN, PROPYLPARABEN

PACKAGE FRONT AND BACK LABELS

12 OZ FRONT AND BACK LABELS: equaline12.jpg